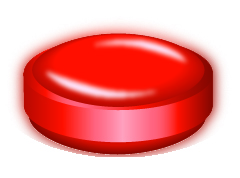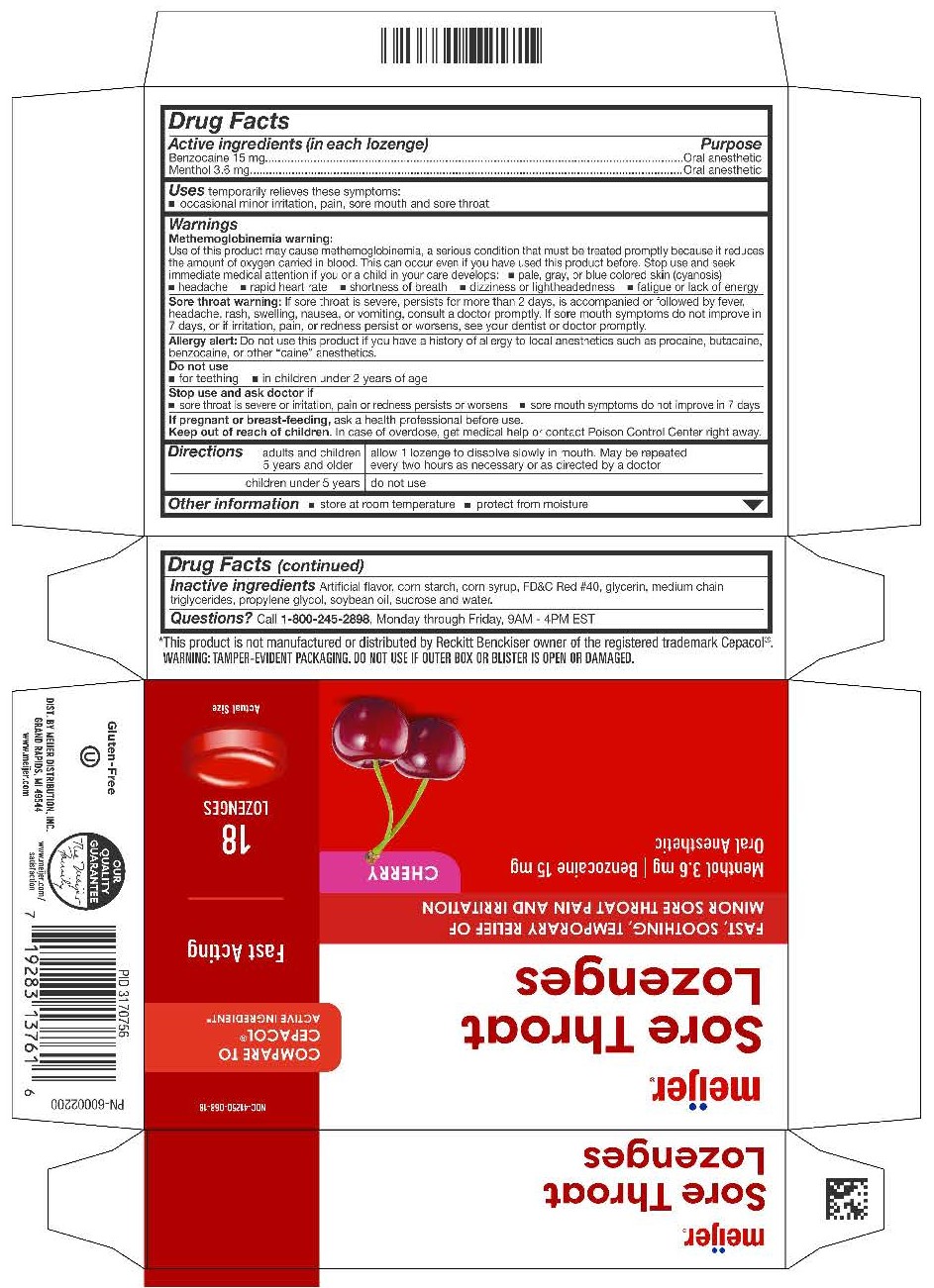 DRUG LABEL: Cherry Sore Throat Lozenges
NDC: 41250-068 | Form: LOZENGE
Manufacturer: Meijer Distribution Inc.
Category: otc | Type: HUMAN OTC DRUG LABEL
Date: 20260202

ACTIVE INGREDIENTS: BENZOCAINE 15 mg/1 1; MENTHOL 3.6 mg/1 1
INACTIVE INGREDIENTS: SUCROSE

Menthol 3.6mg
Benzocaine 15mg

Active Ingredients (in each lozenge)

Benzocaine 15mg

Menthol 3.6mg

Purpose

Oral anesthetic

Oral anesthetic

INDICATIONS AND USAGE

Uses - temporarily relieves these symptoms

occasional minor irritation, pain, sore mouth and sore throat

Warnings

Methemoglobinemia warning:

Use of this product may cause methemoglobinemia, a serious condition that must be treated promptly because it reduces the amount of oxygen carried in blood. This can occur even if you have used this product before. Stop use and seek immediate medical attention if you or a child in your care develops:

- pale, gray, or blue colored skin (cyanosis)
- headache
- rapid heart rate
- shortness of breath
- dizziness or lightheadedness
- fatigue or lack of energy

Sore throat warning: If sore throat is severe, persists for more than 2 days, is accompanied or followed by fever, headache, rash, swelling, nausea, or vomiting, consult a doctor promptly. If sore mouth symptoms do not improve in 7 days, or if irritation, pain, or redness persists or worsens, see your dentist or doctor promptly.

Allergy alert: Do not use this product if you have a history of allergy to local anesthetics such as procaine, butacaine, benzocaine, or other "caine" anesthetics.

Do not use

- for teething
- in children under 2 years of age

Stop use and ask a doctor if

- sore throat is severe or irritation, pain or redness persists or worsens
- sore mouth symptoms do not improve is 7 days

PREGNANCY OR BREAST FEEDING

If Pregnant or breast-feeding, ask a health professional before use.

Keep out of reach of children.

OVERDOSAGE

In case of overdose, get medical help or contact a Poison Control Center right away.

Directions

adults and children 5 years and older - allow 1 lozenge to dissolve slowly in mouth. May be repeated every two hours as necessary or as directed by a doctor

children under 5 years - do not use

Other information

- store at room temperature
- protect from moisture

Inactive Ingredients

Corn starch, FD&C red #40, glucose syrup, glycerin, medium chain triglycerides, natural and artificial flavors, propylene glycol, soybean oil, sucrose, and water.

QUESTIONS

Questions? Call 1-800-245-2898, Monday through Friday, 9AM - 4PM EST